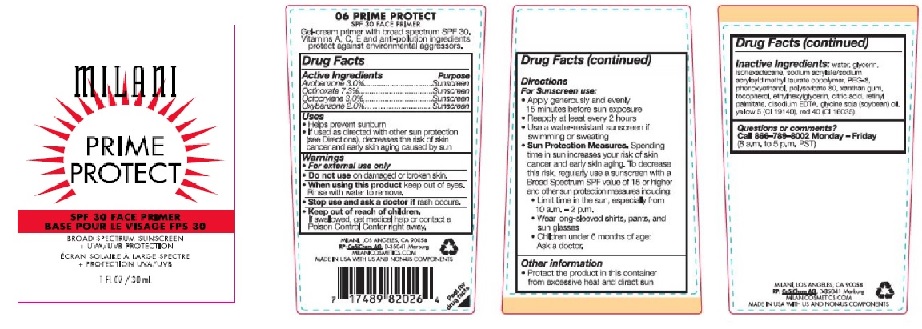 DRUG LABEL: Milani Prime Protect SPF 30 Face Primer
NDC: 71435-8202 | Form: CREAM
Manufacturer: The Milani Group, Inc.
Category: otc | Type: HUMAN OTC DRUG LABEL
Date: 20241204

ACTIVE INGREDIENTS: AVOBENZONE 30 mg/1 mL; OCTINOXATE 73 mg/1 mL; OCTOCRYLENE 30 mg/1 mL; OXYBENZONE 20 mg/1 mL
INACTIVE INGREDIENTS: WATER; GLYCERIN; ISOHEXADECANE; SODIUM ACRYLATE/SODIUM ACRYLOYLDIMETHYLTAURATE COPOLYMER (4000000 MW); PEG-8 STEARATE; PHENOXYETHANOL; POLYSORBATE 80; XANTHAN GUM; TOCOPHEROL; CITRIC ACID MONOHYDRATE; VITAMIN A PALMITATE; EDETATE DISODIUM ANHYDROUS; SOYBEAN OIL; SORBITAN MONOOLEATE; BUTYLATED HYDROXYTOLUENE

Milani Prime Protect SPF 30 Face Primer

Drug Facts

ACTIVE INGREDIENT

Active Ingredients | Purpose
Avobenzone 3.0% | Sunscreen
Octinoxate 7.3% | Sunscreen
Octocrylene 3.0% | Sunscreen
Oxybenzone 2.0% | Sunscreen

Uses

- Helps prevent sunburn
- If used as directed with other sun protection (see Directions), decreases the risk of skin cancer and early skin aging caused by sun

Warnings

- For external use only

- Do not use on damaged or broken skin.

- When using this product keep out of eyes. Rinse with water to remove.

- Stop use and ask a doctor if rash occurs.

- Keep out of reach of children. If swallowed, get medical help or contact a Poison Control Center right away.

Directions

For Sunscreen use:

- Apply generously and evenly 15 minutes before sun exposure
- Reapply at least every 2 hours
- Use a water-resistant sunscreen if swimming or sweating
- Sun Protection Measures. Spending time in sun increases your risk of skin cancer and early skin aging. To decrease this risk, regularly use a sunscreen with a Broad Spectrum SPF value of 15 or higher and other sun protection measures including:
  - Limit time in the sun, especially from 10 a.m. – 2 p.m.
  - Wear long-sleeved shirts, pants, and sun glasses
  - Children under 6 months of age: Ask a doctor.

Other information

- Protect the product in this container from excessive heat and direct sun

Inactive Ingredients

water, glycerin, isohexadecane, sodium acrylate/sodium acryloyldimethyl taurate copolymer, PEG-8, phenoxyethanol, polysorbate 80, xanthan gum, tocopherol, ethylhexylglycerin, citric acid, retinyl palmitate, disodium EDTA, glycine soja (soybean) oil, yellow 5 (CI 19140), red 40 (CI 16035).

Questions or comments?

Call 866–789–8002 Monday – Friday (8 a.m. to 5 p.m. PST)

PRINCIPAL DISPLAY PANEL - 30 mL Tube Carton

MILANI

PRIME
PROTECT

SPF 30 FACE PRIMER

BROAD SPECTRUM SUNSCREEN
+ UVA/UVB PROTECTION

1 FL OZ / 30 mL